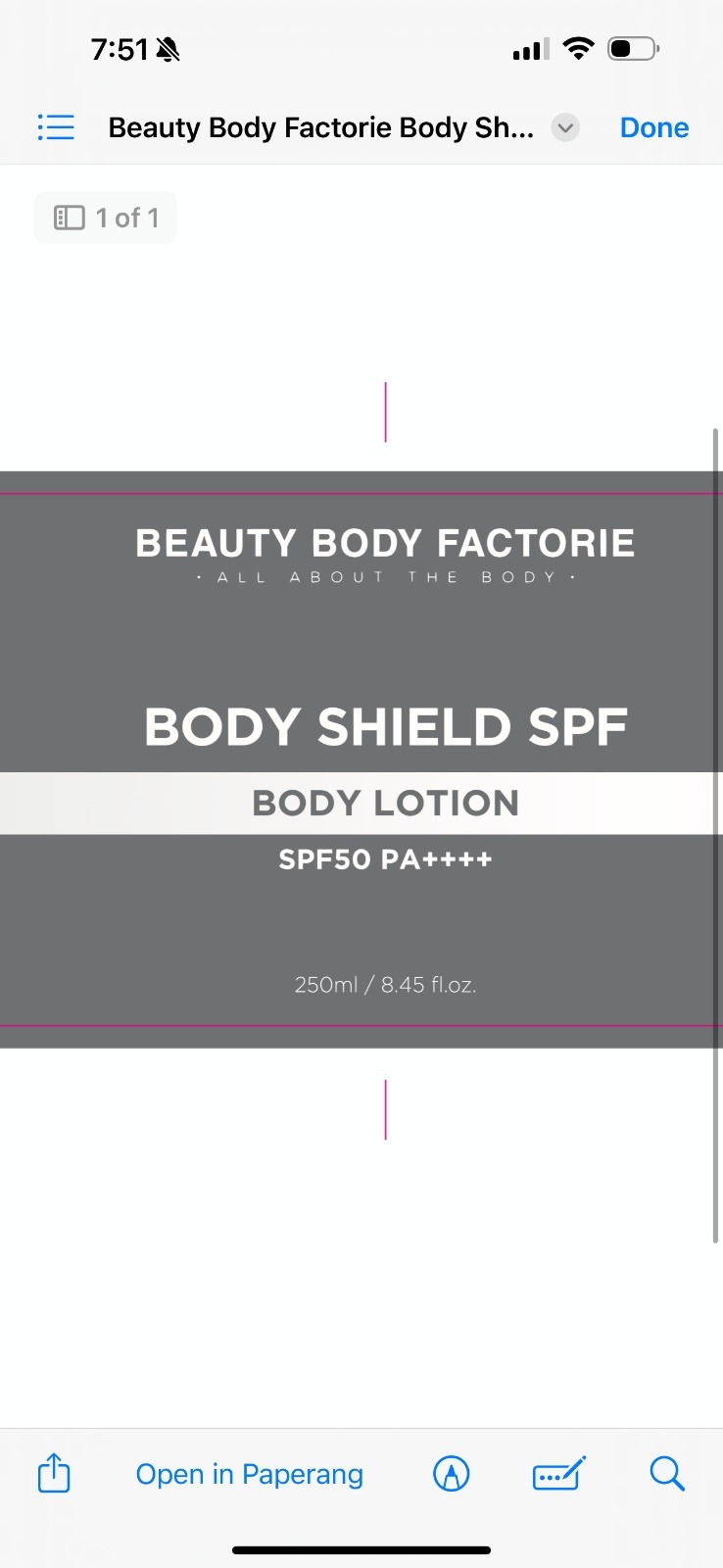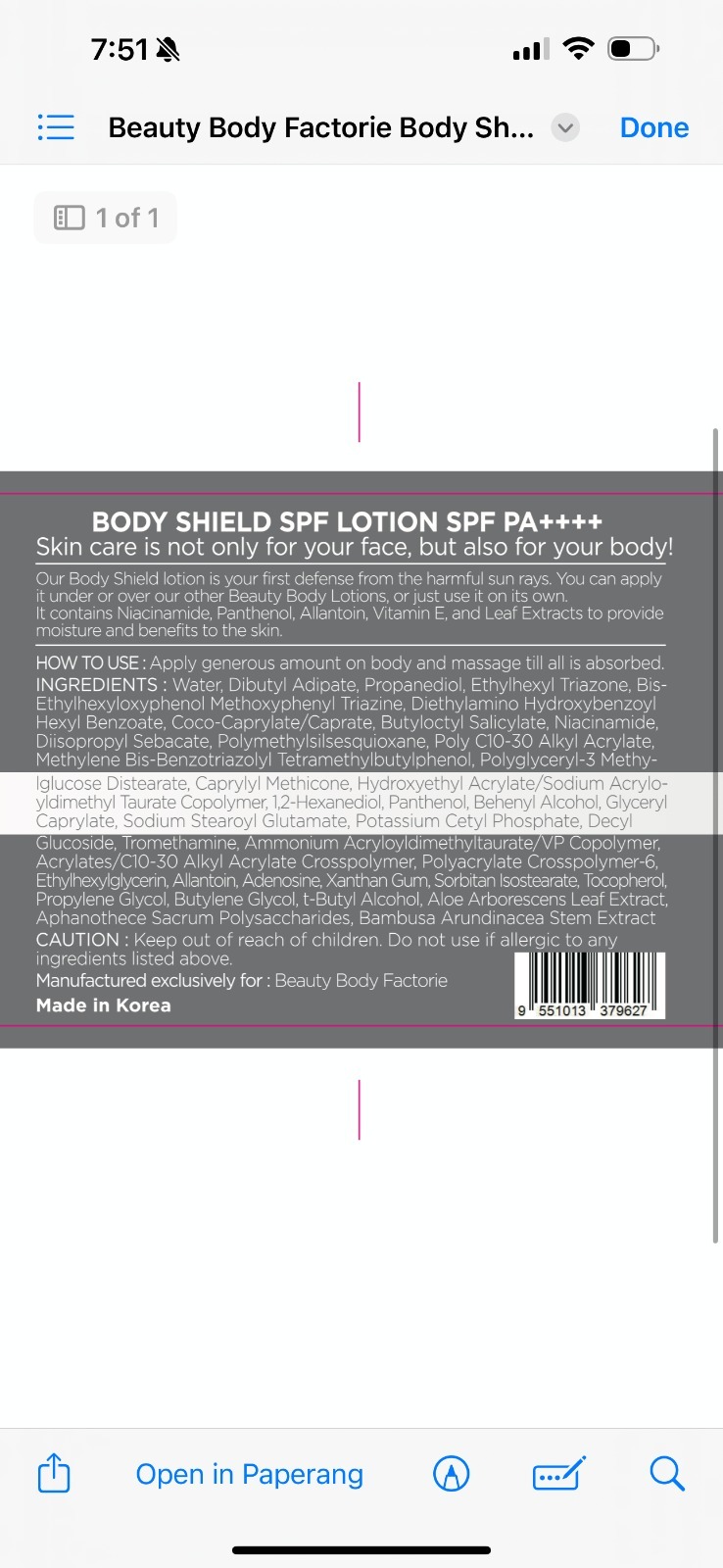 DRUG LABEL: Beauty Body Factorie Body Shield SPF
NDC: 84755-0006 | Form: LOTION
Manufacturer: KRX RESOURCES SDN. BHD.
Category: otc | Type: HUMAN OTC DRUG LABEL
Date: 20251018

ACTIVE INGREDIENTS: METHYLENE BIS-BENZOTRIAZOLYL TETRAMETHYLBUTYLPHENOL 30 mg/1 mL; BIS-ETHYLHEXYLOXYPHENOL METHOXYPHENYL TRIAZINE 30 mg/1 mL; ETHYLHEXYL TRIAZONE 30 mg/1 mL; BUTYLOCTYL SALICYLATE 30 mg/1 mL; DIETHYLAMINO HYDROXYBENZOYL HEXYL BENZOATE 30 mg/1 mL
INACTIVE INGREDIENTS: CAPRYLYL METHICONE; HYDROXYETHYL ACRYLATE/SODIUM ACRYLOYLDIMETHYL TAURATE COPOLYMER (45000 MPA.S AT 1%); TROMETHAMINE; POLYGLYCERYL-3 METHYLGLUCOSE DISTEARATE; BAMBUSA ARUNDINACEA STEM; DIBUTYL ADIPATE; DIISOPROPYL SEBACATE; AMMONIUM ACRYLOYLDIMETHYLTAURATE/VP COPOLYMER; WATER; ETHYLHEXYLGLYCERIN; PROPANEDIOL; 1,2-HEXANEDIOL; SORBITAN ISOSTEARATE; ACRYLATES/C10-30 ALKYL ACRYLATE CROSSPOLYMER (60000 MPA.S); POLYACRYLATE CROSSPOLYMER-6; BEHENYL ALCOHOL; NIACINAMIDE; TOCOPHEROL; SODIUM STEAROYL GLUTAMATE; DECYL GLUCOSIDE; POTASSIUM CETYL PHOSPHATE; BUTYLENE GLYCOL; T-BUTYL ALCOHOL; GLYCERYL CAPRYLATE; COCO-CAPRYLATE/CAPRATE; POLYMETHYLSILSESQUIOXANE (4.5 MICRONS); ALLANTOIN; ADENOSINE; XANTHAN GUM; ALOE BARBADENSIS LEAF; PANTHENOL

PURPOSE

Sunscreen

Helps prevent sunburn

Broad Spectrum UVA/UVB protection

INDICATIONS AND USAGE

Helps protect skin against harmful effects of UVA and UVB rays.

Can be used daily on the body to reduce risk of sun damage, premature aging, and skin dryness caused by sun exposure.

For external use only.

DOSAGE AND ADMINISTRATION

Apply generously and evenly on body 15 minutes before sun exposure.

Reapply at least every 2 hours.

Use a water-resistant sunscreen if swimming or sweating.

For daily use, apply as the last step of skincare, before sun exposure.

WARNINGS

For external use only.

Do not use on damaged or broken skin.

Stop use and consult a doctor if rash or irritation occurs.

Keep out of reach of children. If swallowed, get medical help or contact a Poison Control Center immediately.

Avoid direct contact with eyes. In case of contact, rinse thoroughly with water.

INACTIVE INGREDIENT

Water

Dibutyl Adipate

Propanediol

Coco-Caprylate/Caprate

Niacinamide

Diisopropyl Sebacate

Polymethylsilsesquioxane

Poly C10-30 Alkyl Acrylate

Polyglyceryl-3 Methylglucose Distearate

Caprylyl Methicone

Hydroxyethyl Acrylate/Sodium Acryloyldimethyl Taurate Copolymer

1,2-Hexanediol

Panthenol

Behenyl Alcohol

Glyceryl Caprylate

Sodium Stearoyl Glutamate

Potassium Cetyl Phosphate

Decyl Glucoside

Tromethamine

Ammonium Acryloyldimethyltaurate/VP Copolymer

Acrylates/C10-30 Alkyl Acrylate Crosspolymer

Polyacrylate Crosspolymer-6

Ethylhexylglycerin

Allantoin

Adenosine

Xanthan Gum

Sorbitan Isostearate

Tocopherol (Vitamin E)

Propylene Glycol

Butylene Glycol

t-Butyl Alcohol

Aloe Barbadensis Leaf Extract

Aphanothece Sacrum Polysaccharides

Bambusa Arundinacea Stem Extract

ACTIVE INGREDIENT

Ethylhexyl Triazone

Bis-Ethylhexyloxyphenol Methoxyphenyl Triazine

Diethylamino Hydroxybenzoyl Hexyl Benzoate

Butyloctyl Salicylate

Methylene Bis-Benzotriazolyl Tetramethylbutylphenol

keep out of reach of children

PACKAGE LABEL

Content of labeling